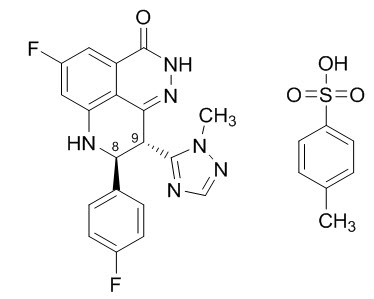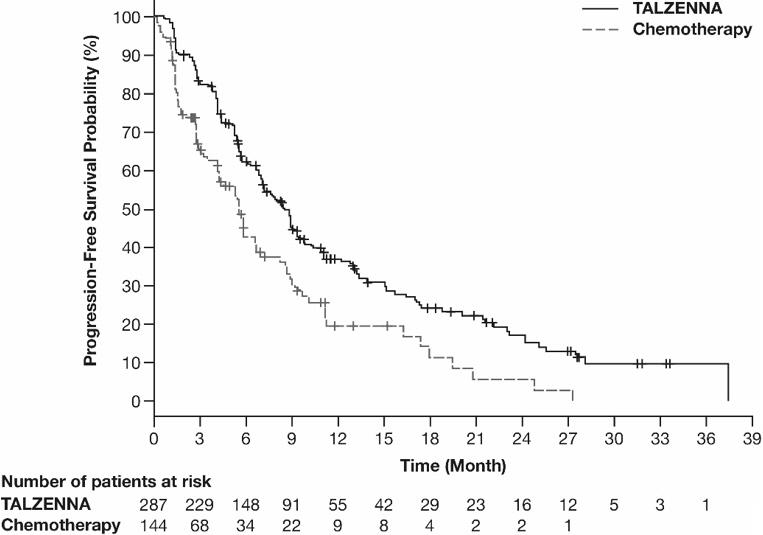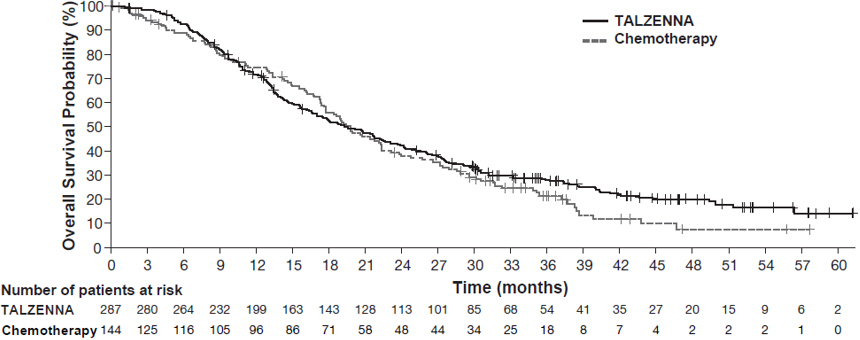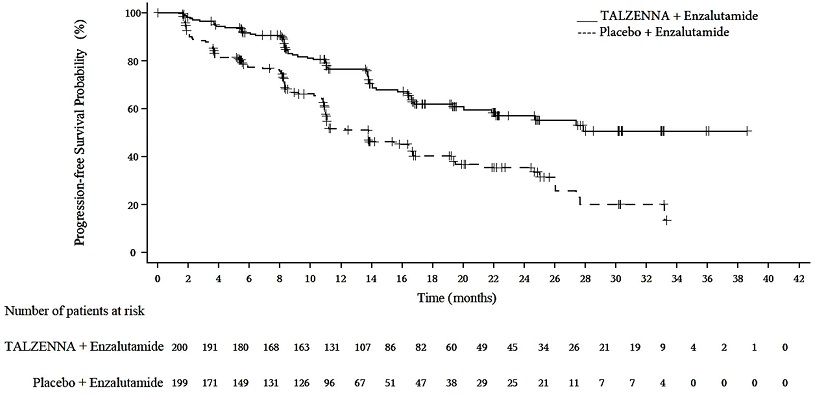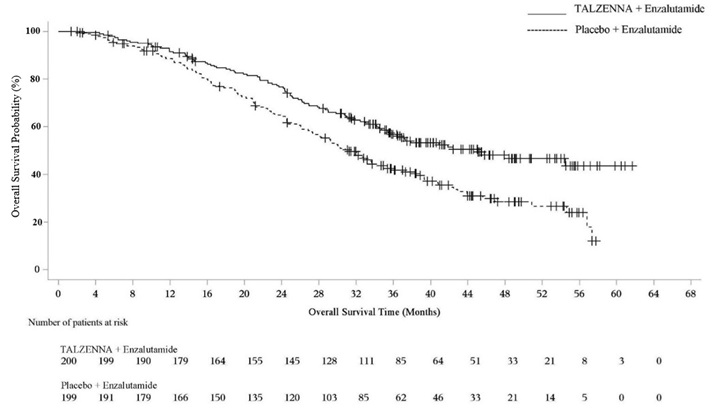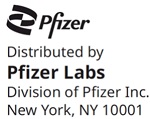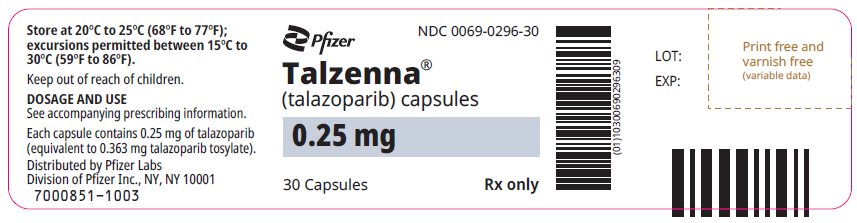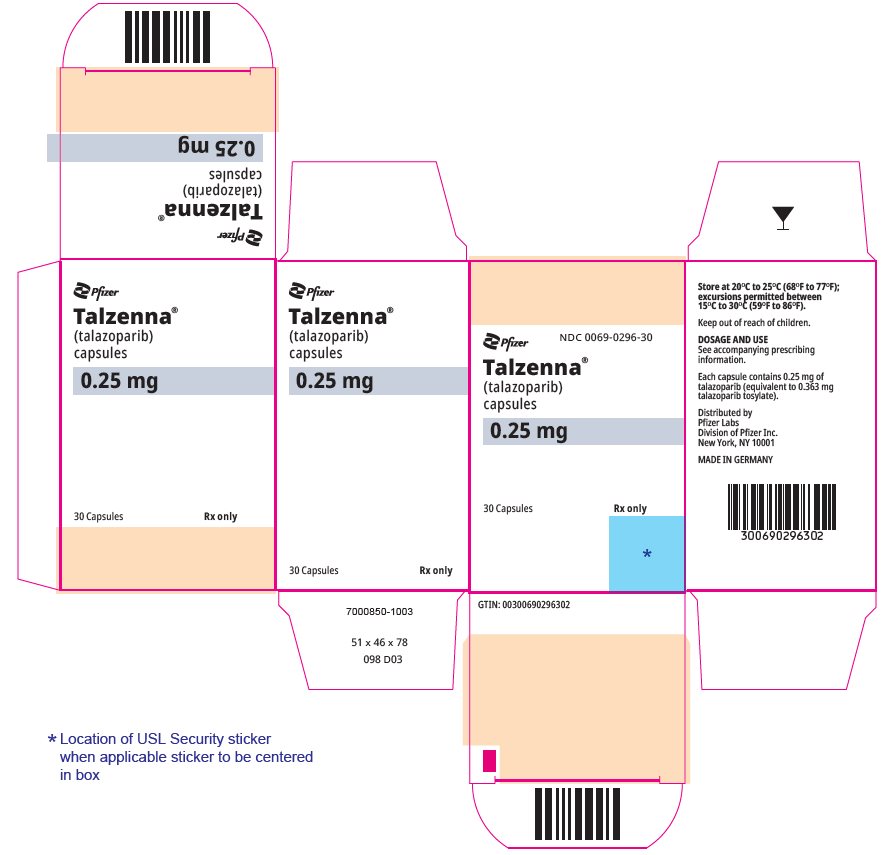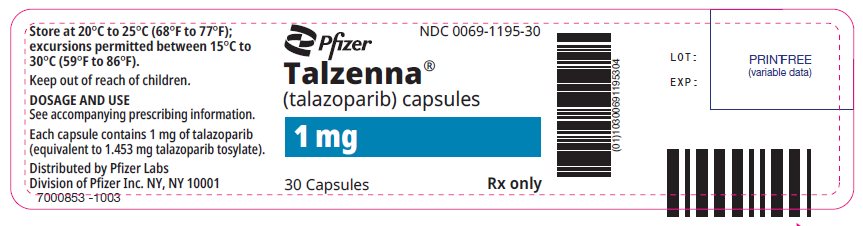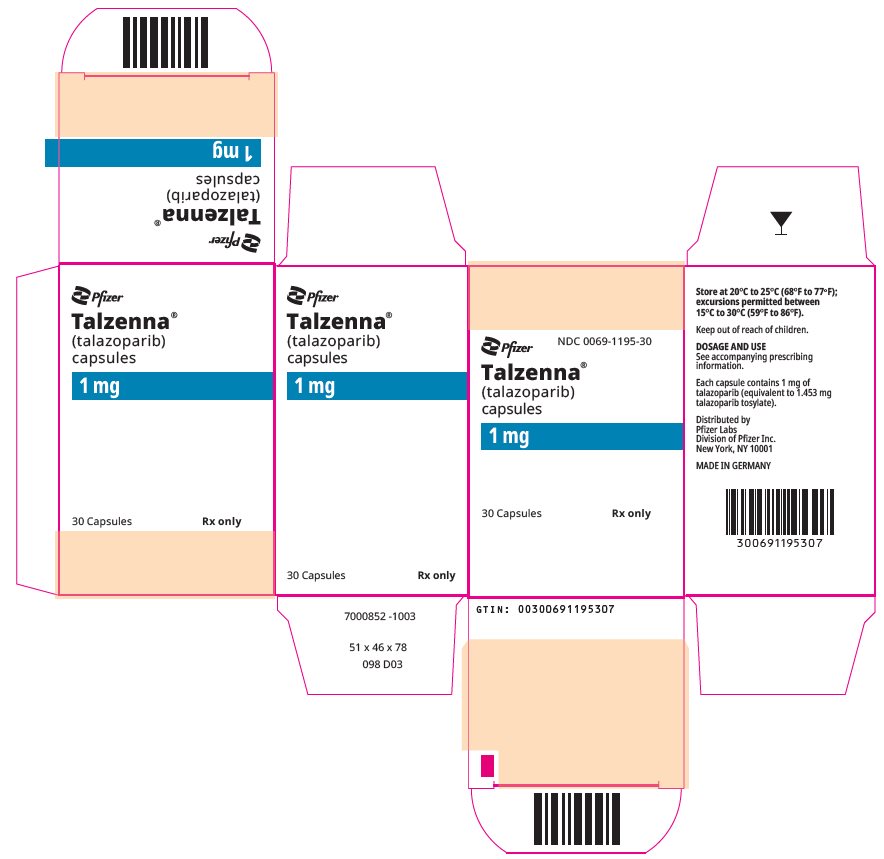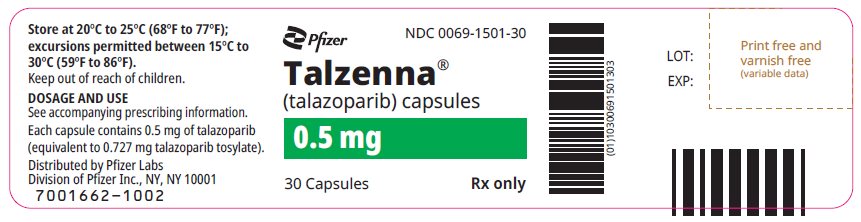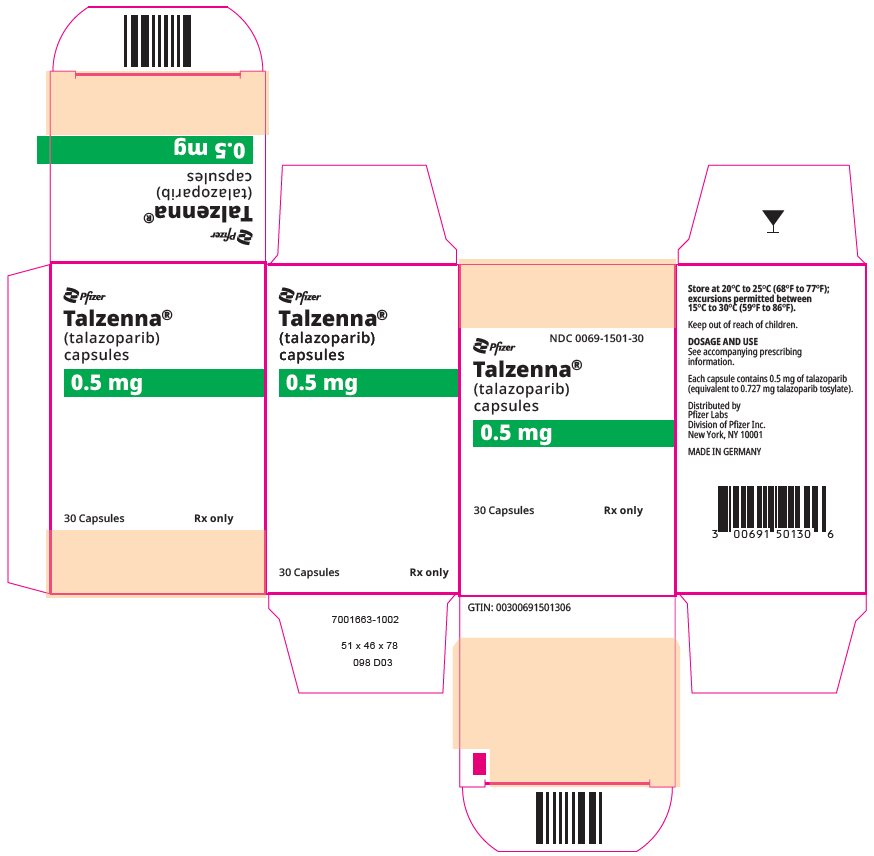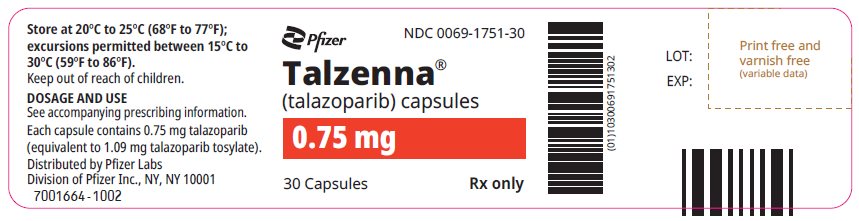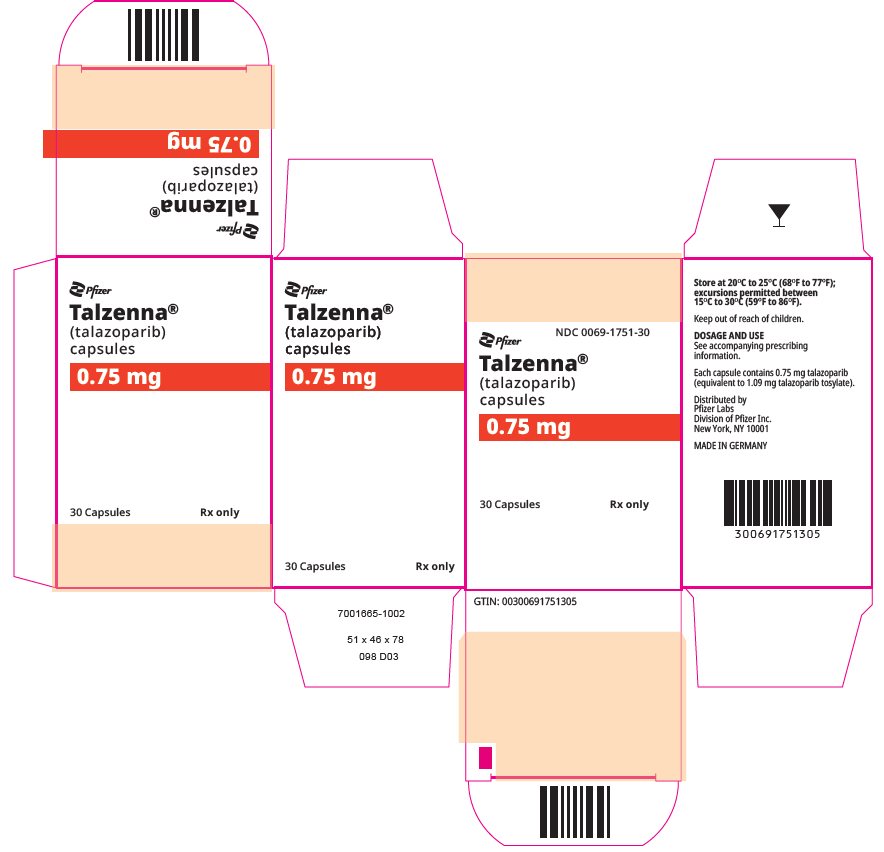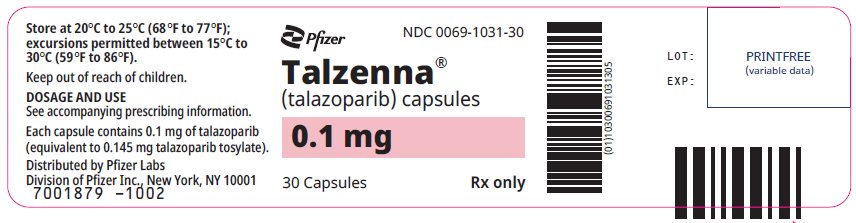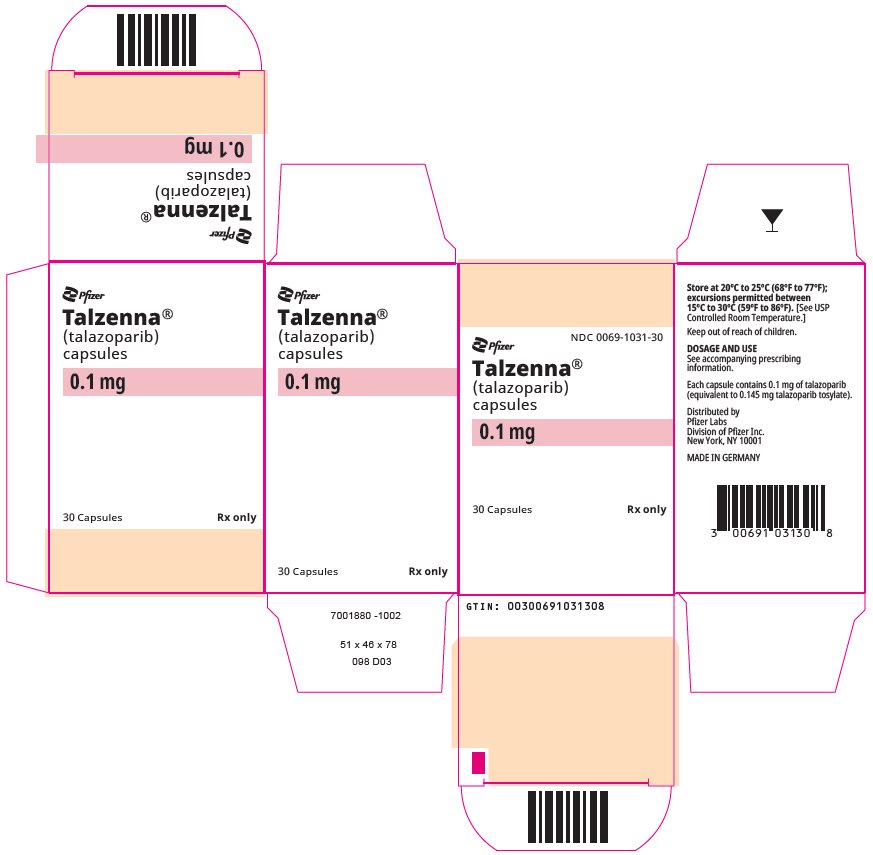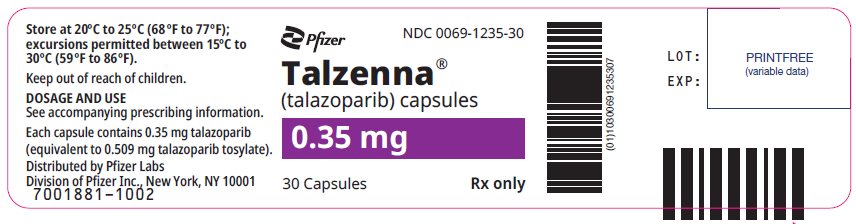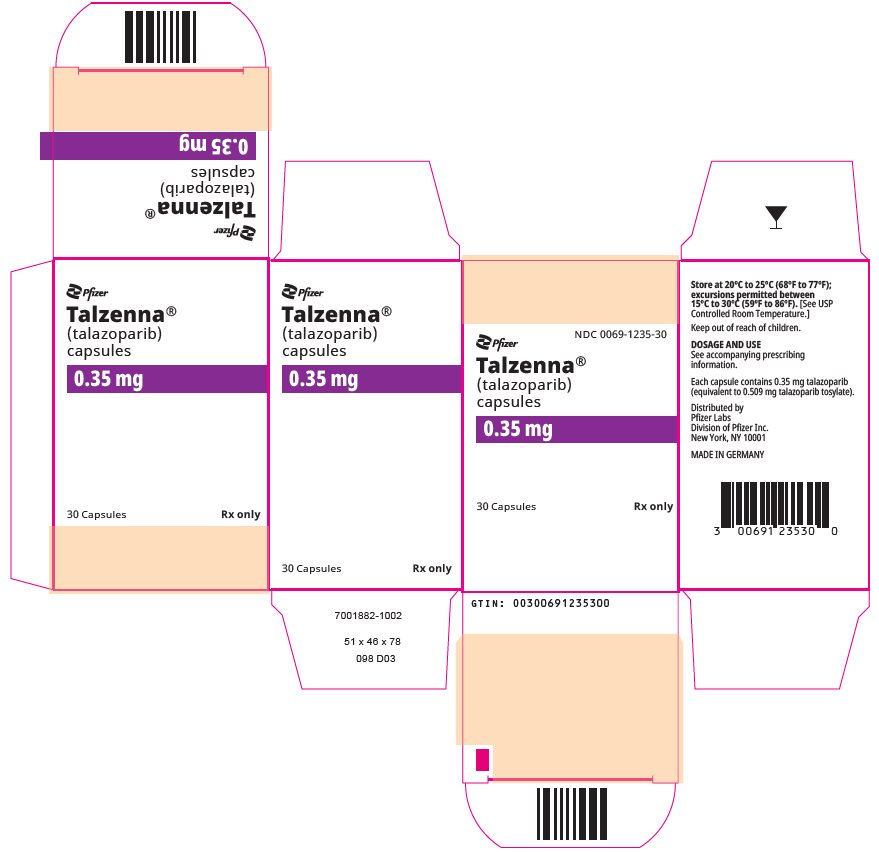 DRUG LABEL: Talzenna
NDC: 0069-0296 | Form: CAPSULE
Manufacturer: Pfizer Laboratories Div Pfizer Inc
Category: prescription | Type: HUMAN PRESCRIPTION DRUG LABEL
Date: 20251218

ACTIVE INGREDIENTS: TALAZOPARIB TOSYLATE 0.25 mg/1 1
INACTIVE INGREDIENTS: MICROCRYSTALLINE CELLULOSE; HYPROMELLOSE, UNSPECIFIED; FERRIC OXIDE YELLOW; FERRIC OXIDE RED; TITANIUM DIOXIDE; SHELLAC; FERROSOFERRIC OXIDE; POTASSIUM HYDROXIDE; AMMONIA; PROPYLENE GLYCOL, (R)-

HIGHLIGHTS OF PRESCRIBING INFORMATION

These highlights do not include all the information needed to use TALZENNA safely and effectively. See full prescribing information for TALZENNA.
TALZENNA® (talazoparib) capsules, for oral use
Initial U.S. Approval: 2018

1 INDICATIONS AND USAGE

TALZENNA is a poly (ADP-ribose) polymerase (PARP) inhibitor indicated for:

Breast Cancer

- As a single agent, for the treatment of adult patients with deleterious or suspected deleterious germline BRCA-mutated (gBRCAm) HER2-negative locally advanced or metastatic breast cancer. Select patients for therapy based on an FDA-approved companion diagnostic for TALZENNA. (1.1)

HRR Gene-mutated Metastatic Castration-Resistant Prostate Cancer (mCRPC)

- In combination with enzalutamide for the treatment of adult patients with HRR gene-mutated metastatic castration-resistant prostate cancer (mCRPC). (1.2)

2 DOSAGE AND ADMINISTRATION

- Take TALZENNA with or without food. (2.4)

Breast Cancer

- The recommended dosage of TALZENNA is 1 mg taken orally once daily until disease progression or unacceptable toxicity. (2.2)
- For adverse reactions, consider dosing interruption or dose reduction. (2.5)

HRR Gene-mutated Metastatic Castration-Resistant Prostate Cancer (mCRPC)

- The recommended dosage of TALZENNA is 0.5 mg taken orally once daily with enzalutamide until disease progression or unacceptable toxicity. (2.3)
- Patients should also receive a gonadotropic-releasing hormone (GnRH) analog concurrently or should have had bilateral orchiectomy. (2.3)

3 DOSAGE FORMS AND STRENGTHS

Capsules: 0.1 mg, 0.25 mg, 0.35 mg, 0.5 mg, 0.75 mg, and 1 mg (3)

4 CONTRAINDICATIONS

None. (4)

5 WARNINGS AND PRECAUTIONS

- Myelodysplastic Syndrome/Acute Myeloid Leukemia (MDS/AML): MDS/AML occurred in patients exposed to TALZENNA, and some cases were fatal. Monitor patients for hematological toxicity and discontinue if MDS/AML is confirmed. (5.1)
- Myelosuppression: TALZENNA may affect hematopoiesis and can cause anemia, neutropenia, and/or thrombocytopenia. (5.2)
- Embryo-Fetal Toxicity: TALZENNA can cause fetal harm. Advise of the potential risk to the fetus and to use effective contraception. (5.3, 8.1, 8.3)

6 ADVERSE REACTIONS

Most common adverse reactions (≥20%) as a single agent, including laboratory abnormalities, are:

- Hemoglobin decreased, neutrophils decreased, lymphocytes decreased, platelets decreased, fatigue, glucose increased, aspartate aminotransferase increased, alkaline phosphatase increased, alanine aminotransferase increased, calcium decreased, nausea, headache, vomiting, alopecia, diarrhea, and decreased appetite. (6.1)

Most common adverse reactions (≥10%) in combination with enzalutamide, including laboratory abnormalities, are:

- Hemoglobin decreased, neutrophils decreased, lymphocytes decreased, fatigue, platelets decreased, calcium decreased, nausea, decreased appetite, sodium decreased, phosphate decreased, fractures, magnesium decreased, dizziness, bilirubin increased, potassium decreased, and dysgeusia. (6.1)

To report SUSPECTED ADVERSE REACTIONS, contact Pfizer Inc. at 1-800-438-1985 or FDA at 1-800-FDA-1088 or www.fda.gov/medwatch.

7 DRUG INTERACTIONS

- P-gp Inhibitors: Reduce the dose when coadministered with certain P-gp inhibitors. Monitor for increased adverse reactions. (2.7, 7.1)
- BCRP Inhibitors: Monitor for potential increased adverse reactions. (7.1)

8 USE IN SPECIFIC POPULATIONS

- Lactation: Advise women not to breastfeed. (8.2)
- Renal Impairment: Reduce the dose and monitor for increased adverse reactions for patients with moderate or severe renal impairment. (2.6, 8.7)

FULL PRESCRIBING INFORMATION

1 INDICATIONS AND USAGE

1.1 BRCA-mutated (gBRCAm) HER2-negative Locally Advanced or Metastatic Breast Cancer

TALZENNA is indicated as a single agent for the treatment of adult patients with deleterious or suspected deleterious germline breast cancer susceptibility gene (BRCA)-mutated (gBRCAm) human epidermal growth factor receptor 2 (HER2)-negative locally advanced or metastatic breast cancer. Select patients for therapy based on an FDA-approved companion diagnostic for TALZENNA [see Dosage and Administration (2.1)].

1.2 HRR Gene-mutated Metastatic Castration-Resistant Prostate Cancer (mCRPC)

TALZENNA is indicated in combination with enzalutamide for the treatment of adult patients with homologous recombination repair (HRR) gene-mutated metastatic castration-resistant prostate cancer (mCRPC) [see Dosage and Administration (2.3)].

2 DOSAGE AND ADMINISTRATION

2.1 Patient Selection

Information on the FDA-approved tests for the detection of genetic mutations is available at http://www.fda.gov/companiondiagnostics.

gBRCAm HER2-negative Locally Advanced or Metastatic Breast Cancer

Select patients for the treatment of advanced breast cancer with TALZENNA based on the presence of germline BRCA mutations [see Indications and Usage (1.1), Clinical Studies (14.1)].

HRR Gene-mutated Metastatic Castration-Resistant Prostate Cancer

Select patients for the treatment of HRR gene-mutated mCRPC with TALZENNA based on the presence of alterations in genes directly or indirectly involved in HRR (ATM, ATR, BRCA1, BRCA2, CDK12, CHEK2, FANCA, MLH1, MRE11A, NBN, PALB2, or RAD51C) [see Indications and Usage (1.2), Clinical Studies (14.2)].

An FDA-approved test for the detection of HRR gene mutations for use with TALZENNA is not currently available.

2.2 Recommended Dosage for gBRCAm HER2-negative Locally Advanced or Metastatic Breast Cancer

The recommended dosage of TALZENNA is 1 mg taken orally once daily, until disease progression or unacceptable toxicity.

2.3 Recommended Dosage for HRR Gene-mutated mCRPC

The recommended dosage of TALZENNA is 0.5 mg taken orally once daily with enzalutamide until disease progression or unacceptable toxicity.

Refer to the enzalutamide prescribing information for recommended enzalutamide dosing information.

Patients receiving TALZENNA and enzalutamide should also receive a gonadotropin-releasing hormone (GnRH) analog concurrently or should have had bilateral orchiectomy.

2.4 Administration

Take TALZENNA with or without food.

Swallow TALZENNA capsules whole. Do not open or dissolve.

If a patient vomits or misses a dose of TALZENNA, instruct them to take the next prescribed dose at the usual time.

2.5 Dosage Modifications for Adverse Reactions

To manage adverse reactions, consider interruption of treatment with or without dose reduction based on severity and clinical presentation. Recommended dose reductions are indicated in Table 1 and Table 2. Treatment with TALZENNA should be discontinued if more than 3 dose reductions are required.

gBRCAm HER2-negative Locally Advanced or Metastatic Breast Cancer

Table 1. Dose Reduction Levels for Adverse Reactions—Breast Cancer
Dose Reductions | Dose Level
Recommended starting dose | 1 mg once daily
First dose reduction | 0.75 mg once daily
Second dose reduction | 0.5 mg once daily
Third dose reduction | 0.25 mg once daily

HRR Gene-mutated mCRPC

Table 2. Dose Reduction Levels for Adverse Reactions—mCRPC
Dose Reductions | Dose Level
Recommended starting dose | 0.5 mg once daily
First dose reduction | 0.35 mg once daily
Second dose reduction | 0.25 mg once daily
Third dose reduction | 0.1 mg once daily

Refer to the enzalutamide prescribing information for dose modifications for adverse reactions associated with enzalutamide.

gBRCAm HER2-negative Locally Advanced or Metastatic Breast Cancer and HRR Gene-mutated mCRPC

Monitor complete blood counts monthly and as clinically indicated [see Warnings and Precautions (5.2)].

Table 3. Dose Modification and Management for Adverse Reactions
Adverse Reactions | Withhold TALZENNA Until Levels Resolve to | Resume TALZENNA
Hemoglobin <8 g/dL | ≥9 g/dL | Resume TALZENNA at a reduced dose
Platelet count <50,000/μL | ≥75,000/μL | Resume TALZENNA at a reduced dose
Neutrophil count <1,000/μL | ≥1500/µL | Resume TALZENNA at a reduced dose
Non-hematologic Grade 3 or Grade 4 | ≤Grade 1 | Consider resuming TALZENNA at a reduced dose or discontinue

2.6 Recommended Dosage in Patients with Renal Impairment

gBRCAm HER2-negative Locally Advanced or Metastatic Breast Cancer

The recommended dosage of TALZENNA for patients with moderate renal impairment (CLcr 30 - 59 mL/min) is 0.75 mg taken orally once daily [see Use in Specific Populations (8.7)].

The recommended dosage of TALZENNA for patients with severe renal impairment (CLcr 15 - 29 mL/min) is 0.5 mg taken orally once daily [see Use in Specific Populations (8.7)].

HRR Gene-mutated mCRPC

The recommended dosage of TALZENNA for patients with moderate renal impairment (CLcr 30 - 59 mL/min) is 0.35 mg taken orally once daily with enzalutamide [see Use in Specific Populations (8.7)].

The recommended dosage of TALZENNA for patients with severe renal impairment (CLcr 15 - 29 mL/min) is 0.25 mg taken orally once daily with enzalutamide [see Use in Specific Populations (8.7)].

2.7 Dosage Modifications for P-glycoprotein Inhibitors

gBRCAm HER2-negative Locally Advanced or Metastatic Breast Cancer

Avoid coadministration of TALZENNA with the following P-glycoprotein (P-gp) inhibitors: itraconazole, amiodarone, carvedilol, clarithromycin, itraconazole, and verapamil. If coadministration of TALZENNA with these P-gp inhibitors cannot be avoided, reduce the dose of TALZENNA to 0.75 mg taken orally once daily. When the P-gp inhibitor is discontinued, increase the dose of TALZENNA (after 3 – 5 half-lives of the P-gp inhibitor) to the dose of TALZENNA that was used before starting the P-gp inhibitor [see Drug Interactions (7.1)].

Monitor for increased adverse reactions and modify the dosage as recommended for adverse reactions when TALZENNA is coadministered with other P-gp inhibitors [see Dosage and Administration (2.5)].

3 DOSAGE FORMS AND STRENGTHS

Table 4. Dosage Forms and Strengths
Capsule Strength | Description
0.1 mg | White cap (printed with “Pfizer” in black) and a white body (printed with “TLZ 0.1” in black)
0.25 mg | Ivory cap (printed with “Pfizer” in black) and a white body (printed with “TLZ 0.25” in black)
0.35 mg | Ivory cap (printed with “Pfizer” in black) and an ivory body (printed with “TLZ 0.35” in black)
0.5 mg | Light pink cap (printed with “Pfizer” in black) and a white body (printed with “TLZ 0.5” in black)
0.75 mg | Light orange cap (printed with “Pfizer” in black) and a white body (printed with “TLZ 0.75” in black)
1 mg | Light red cap (printed with “Pfizer” in black) and a white body (printed with “TLZ 1” in black)

4 CONTRAINDICATIONS

None.

5 WARNINGS AND PRECAUTIONS

5.1 Myelodysplastic Syndrome/Acute Myeloid Leukemia

Myelodysplastic Syndrome/Acute Myeloid Leukemia (MDS/AML), including cases with a fatal outcome, has been reported in patients who received TALZENNA.

Overall, MDS/AML has been reported in 0.4% (3 out of 788) of solid tumor patients treated with TALZENNA as a single agent in clinical studies. In TALAPRO-2, MDS/AML occurred in 2 out of 511 (0.4%) patients treated with TALZENNA and enzalutamide and in 0 out of 517 (0%) patients treated with placebo and enzalutamide [see Adverse Reactions (6.1)]. The durations of TALZENNA treatment in these 5 patients prior to developing MDS/AML were 0.3, 1, 2, 3, and 5 years. Most of these patients had received previous chemotherapy with platinum agents and/or other DNA damaging agents including radiotherapy.

Do not start TALZENNA until patients have adequately recovered from hematological toxicity caused by previous chemotherapy. Monitor blood counts monthly during treatment with TALZENNA. For prolonged hematological toxicities, interrupt TALZENNA and monitor blood counts weekly until recovery. If counts do not recover within 4 weeks, refer the patient to a hematologist for further investigations including bone marrow analysis and blood sample for cytogenetics. If MDS/AML is confirmed, discontinue TALZENNA.

5.2 Myelosuppression

Myelosuppression consisting of anemia, neutropenia, and/or thrombocytopenia, have been reported in patients treated with TALZENNA [see Adverse Reactions (6.1)].

Grade ≥3 anemia, neutropenia, and thrombocytopenia were reported, respectively, in 39%, 21%, and 15% of patients receiving TALZENNA as a single agent. Discontinuation due to anemia, neutropenia, and thrombocytopenia occurred, respectively, in 0.7%, 0.3%, and 0.3% of patients.

In TALAPRO-2, Grade ≥3 anemia, neutropenia, and thrombocytopenia were reported, respectively, in 48%, 19%, and 9% of patients receiving TALZENNA and enzalutamide. Forty-two percent of patients (216/511) required a red blood cell transfusion, including 25% (127/511) who required more than one transfusion. Discontinuation due to anemia, neutropenia, and thrombocytopenia occurred, respectively, in 8%, 3%, and 0.4% of patients.

Withhold TALZENNA until patients have adequately recovered from hematological toxicity caused by previous therapy. Monitor blood counts monthly during treatment with TALZENNA. If hematological toxicities do not resolve within 28 days, discontinue TALZENNA and refer the patient to a hematologist for further investigations including bone marrow analysis and blood sample for cytogenetics [see Dosage and Administration (2.5)].

5.3 Embryo-Fetal Toxicity

Based on its mechanism of action and findings from animal data, TALZENNA can cause fetal harm when administered to a pregnant woman. In an animal reproduction study, administration of talazoparib to pregnant rats during the period of organogenesis caused fetal malformations and structural skeletal variations, and embryo-fetal death at exposures that were 0.24 times the area under the concentration-time curve (AUC) in patients receiving the recommended human dose of 1 mg daily. Apprise pregnant women and females of reproductive potential of the potential risk to a fetus. Advise females of reproductive potential to use effective contraception during treatment and for 7 months following the last dose of TALZENNA [see Use in Specific Populations (8.1, 8.3), Clinical Pharmacology (12.1)].

Based on findings from genetic toxicity and animal reproduction studies, advise male patients with female partners of reproductive potential or who are pregnant to use effective contraception during treatment and for 4 months following the last dose of TALZENNA [see Use in Specific Populations (8.1, 8.3), Nonclinical Toxicology (13.1)].

6 ADVERSE REACTIONS

The following clinically significant adverse reactions are described elsewhere in the labeling:

- Myelodysplastic Syndrome/Acute Myeloid Leukemia [see Warnings and Precautions (5.1)]
- Myelosuppression [see Warnings and Precautions (5.2)]

6.1 Clinical Trials Experience

Because clinical trials are conducted under widely varying conditions, adverse reaction rates observed in the clinical trials of a drug cannot be directly compared to rates in the clinical trials of another drug and may not reflect the rates observed in practice.

The data described in the WARNINGS AND PRECAUTIONS section reflect exposure to single agent TALZENNA in solid tumor clinical studies, including 286 patients enrolled in EMBRACA trial and to TALZENNA 0.5 mg daily with enzalutamide in 511 patients enrolled in the TALAPRO-2 trial that included 197 patients with HRR gene-mutated mCRPC.

gBRCAm HER2-negative Locally Advanced or Metastatic Breast Cancer

EMBRACA

The safety of TALZENNA as a single agent was evaluated in gBRCAm patients with HER2-negative locally advanced or metastatic breast cancer who had previously received no more than 3 lines of chemotherapy for the treatment of locally advanced/metastatic disease [see Clinical Studies (14.1)]. EMBRACA was a randomized, open-label, multi-center study in which 412 patients received either TALZENNA 1 mg once daily (N=286) or a chemotherapy agent (capecitabine, eribulin, gemcitabine, or vinorelbine) of the healthcare provider's choice (N=126) until disease progression or unacceptable toxicity. The median duration of study treatment was 6.1 months in patients who received TALZENNA and 3.9 months in patients who received chemotherapy.

Serious adverse reactions of TALZENNA occurred in 32% of patients. Serious adverse reactions reported in >2% of patients included anemia (6%) and pyrexia (2%). Fatal adverse reactions occurred in 1% of patients, including cerebral hemorrhage, liver disorder, veno-occlusive liver disease, and worsening neurological symptoms (1 patient each).

Permanent discontinuation due to adverse reactions occurred in 5% of TALZENNA patients. Dosing interruptions due to an adverse reaction of any grade occurred in 65% of patients receiving TALZENNA; dose reductions due to any cause occurred in 53% of TALZENNA patients.

The most common (≥20%) adverse reactions, including laboratory abnormalities, were hemoglobin decreased, neutrophils decreased, lymphocytes decreased, platelets decreased, fatigue, glucose increased, aspartate aminotransferase increased, alkaline phosphatase increased, alanine aminotransferase increased, calcium decreased, nausea, headache, vomiting, alopecia, diarrhea, and decreased appetite.

Table 5 and Table 6 summarize the most common adverse reactions and laboratory abnormalities, respectively, in patients treated with TALZENNA or chemotherapy in the EMBRACA study.

Table 5. Adverse Reactions [Graded according to NCI CTCAE 4.03.] (≥20%) in Patients Receiving TALZENNA in EMBRACA
Adverse Reactions | TALZENNA N=286 (%) |  |  | Chemotherapy N=126 (%)
Adverse Reactions | Grades 1–4 | Grade 3 | Grade 4 | Grades 1–4 | Grade 3 | Grade 4
General Disorders and Administration Site Conditions
Fatigue [Includes fatigue and asthenia.] | 62 | 3 | 0 | 50 | 5 | 0
Gastrointestinal Disorders
Nausea | 49 | 0.3 | 0 | 47 | 2 | 0
Vomiting | 25 | 2 | 0 | 23 | 2 | 0
Diarrhea | 22 | 1 | 0 | 26 | 6 | 0
Nervous System Disorders
Headache | 33 | 2 | 0 | 22 | 1 | 0
Skin and Subcutaneous Tissue Disorders
Alopecia | 25 | 0 | 0 | 28 | 0 | 0
Metabolism and Nutrition Disorders
Decreased appetite | 21 | 0.3 | 0 | 22 | 1 | 0
Abbreviation: N=number of patients.

Clinically relevant adverse reactions in <20% of patients who received TALZENNA included abdominal pain (19%), dizziness (17%), dysgeusia (10%), dyspepsia (10%), stomatitis (8%), and febrile neutropenia (0.3%).

Table 6. Select Laboratory Abnormalities (≥25%) of Patients in EMBRACA
 | TALZENNA N [This number represents the safety population. The derived values in the table are based on the total number of evaluable patients for each laboratory parameter.] =286 (%) |  |  | Chemotherapy N=126 (%)
Parameter | Grades 1–4 | Grade 3 | Grade 4 | Grades 1–4 | Grade 3 | Grade 4
Hemoglobin decreased | 90 | 39 | 0 | 77 | 6 | 0
Neutrophils decreased | 68 | 17 | 3 | 70 | 21 | 17
Lymphocytes decreased | 76 | 17 | 0.7 | 53 | 8 | 0.8
Platelets decreased | 55 | 11 | 4 | 29 | 2 | 0
Glucose increased [This number represents non-fasting glucose.] | 54 | 2 | 0 | 51 | 2 | 0
Aspartate aminotransferase Increased | 37 | 2 | 0 | 48 | 3 | 0
Alkaline phosphatase increased | 36 | 2 | 0 | 34 | 2 | 0
Alanine aminotransferase increased | 33 | 1 | 0 | 37 | 2 | 0
Calcium decreased | 28 | 1 | 0 | 16 | 0 | 0
Abbreviation: N=number of patients.

HRR Gene-mutated mCRPC

The safety of TALZENNA with enzalutamide was evaluated in patients with HRR gene-mutated mCRPC enrolled in TALAPRO-2 [see Clinical Studies (14.2)]. Patients were randomized to receive either TALZENNA 0.5 mg with enzalutamide 160 mg once daily (n=197), or placebo with enzalutamide 160 mg once daily (n=199) until disease progression or unacceptable toxicity. Among patients receiving TALZENNA, 86% were exposed for 6 months or longer, 60% were exposed for greater than one year, and 18% were exposed for greater than two years.

Serious adverse reactions of TALZENNA with enzalutamide occurred in 30% of patients. Serious adverse reactions reported in >2% of patients included anemia (9%) and fracture (3%). Fatal adverse reactions occurred in 1.5% of patients, including pneumonia, COVID infection, and sepsis (1 patient each).

Permanent discontinuation of TALZENNA due to adverse reactions occurred in 10% of patients treated in the TALZENNA with enzalutamide arm. The most common adverse reactions which resulted in permanent discontinuation of TALZENNA were anemia (4%), fatigue, bone fracture, ischemic heart disease, and spinal cord compression (1% each).

Dosage interruption of TALZENNA due to adverse reactions occurred in 58% of patients treated in the TALZENNA with enzalutamide arm. The most common adverse reactions which resulted in dose interruption of TALZENNA were anemia (42%), neutropenia (15%), and platelet count decreased (9%) and fatigue (5%).

Dose reduction of TALZENNA due to adverse reactions occurred in 52% of patients treated in the TALZENNA with enzalutamide arm. The most common adverse reactions which resulted in dose reduction of TALZENNA were anemia (43%), neutrophil count decreased (15%), platelet count decreased (6%), and fatigue (4%).

The most common adverse reactions (≥10%), including laboratory abnormalities, in patients who received TALZENNA with enzalutamide were hemoglobin decreased, neutrophils decreased, lymphocytes decreased, fatigue, platelets decreased, calcium decreased, nausea, decreased appetite, sodium decreased, phosphate decreased, fractures, magnesium decreased, dizziness, bilirubin increased, potassium decreased, and dysgeusia.

Table 7 and Table 8 summarize the most common adverse reactions and laboratory abnormalities, respectively, in the TALAPRO-2 study.

Table 7. Adverse Reactions [Graded according to NCI CTCAE 4.03.] (≥10%) in Patients Receiving TALZENNA (with a Difference Between Arms of ≥2%) in TALAPRO-2
 | TALZENNA with Enzalutamide; N=197 |  |  | Placebo with Enzalutamide; N=199
 | Grades 1-4; % | Grade 3; % | Grade 4; % | Grades 1-4; % | Grade 3; % | Grade 4; %
Fatigue [Includes fatigue and asthenia.] | 49 | 4 | 0 | 40 | 1 | 0
Nausea | 21 | 2 | 0 | 17 | 1 | 0.5
Decreased appetite | 20 | 1 | 0 | 14 | 1 | 1
Fractures [Fractures include multiple similar terms.] | 14 | 3 | 0 | 10 | 1.5 | 0
Dizziness [Includes dizziness, dizziness postural, vertigo.] | 13 | 1.5 | 0 | 9 | 1.5 | 0
Dysgeusia [Includes ageusia, anosmia, dysgeusia.] | 10 | 0 | 0 | 4.5 | 0 | 0
Abbreviation: N=number of patients.

Clinically relevant adverse reactions in <10% of patients who received TALZENNA with enzalutamide included abdominal pain (9%), vomiting (9%), alopecia (7%), dyspepsia (4%), venous thromboembolism (3%) and stomatitis (2%).

Table 8. Select Laboratory Abnormalities (≥10%) That Worsened from Baseline in Patients Who Received TALZENNA in TALAPRO-2
Laboratory Abnormality | TALZENNA with Enzalutamide; N=197 [The denominator used to calculate the rate varied from 198 to 199 in the placebo with enzalutamide arm based on the number of patients with a baseline value and at least one post-treatment value.] |  |  | Placebo with Enzalutamide; N=199
Laboratory Abnormality | Grades 1‑4; % | Grade 3; % | Grade 4; % | Grades 1‑4; % | Grade 3; % | Grade 4; %
Hemoglobin decreased | 79 | 41 | 0 | 34 | 6 | 0
Neutrophils decreased | 60 | 18 | 1 | 18 | 0 | 1
Lymphocytes decreased | 58 | 13 | 0 | 36 | 7 | 0
Platelets decreased | 45 | 6 | 3 | 8 | 0.5 | 0
Calcium decreased | 25 | 0 | 1 | 11 | 0 | 1
Sodium decreased | 22 | 3 | 0 | 20 | 1.5 | 0
Phosphate decreased | 17 | 3 | 1 | 13 | 2 | 0
Magnesium decreased | 14 | 0 | 1 | 12 | 0 | 0.5
Bilirubin increased | 11 | 0.5 | 0 | 7 | 0 | 0
Potassium decreased | 11 | 0 | 1 | 7 | 1 | 0.5
Abbreviation: N=number of patients.

7 DRUG INTERACTIONS

7.1 Effect of Other Drugs on TALZENNA

Effect of P-gp Inhibitors
Breast Cancer
Avoid coadministration of TALZENNA with the following P-gp inhibitors: itraconazole, amiodarone, carvedilol, clarithromycin, itraconazole, and verapamil. If coadministration of TALZENNA with these P-gp inhibitors cannot be avoided, reduce the dose of TALZENNA [see Dosage and Administration (2.7)]. When the P-gp inhibitor is discontinued, increase the dose of TALZENNA [see Dosage and Administration (2.7)].

Coadministration of TALZENNA with these P-gp inhibitors increased talazoparib concentrations [see Clinical Pharmacology (12.3)], which may increase the risk of adverse reactions.

Monitor for increased adverse reactions and modify the dosage as recommended for adverse reactions when TALZENNA is coadministered with other P-gp inhibitors [see Dosage and Administration (2.5)].

HRR Gene-mutated mCRPC
The effect of coadministration of P-gp inhibitors on talazoparib exposure when TALZENNA is taken with enzalutamide has not been studied. Monitor patients for increased adverse reactions and modify the dosage as recommended for adverse reactions when TALZENNA is coadministered with a P-gp inhibitor [see Dosage and Administration (2.5)].

Effect of Breast Cancer Resistance Protein (BCRP) Inhibitors

Monitor patients for increased adverse reactions and modify the dosage as recommended for adverse reactions when TALZENNA is coadministered with a BCRP inhibitor [see Dosage and Administration (2.5)].

Coadministration of TALZENNA with BCRP inhibitors may increase talazoparib exposure [see Clinical Pharmacology (12.3)], which may increase the risk of adverse reactions.

8 USE IN SPECIFIC POPULATIONS

8.1 Pregnancy

Risk Summary
Based on findings from animal studies and its mechanism of action [see Clinical Pharmacology (12.1)], TALZENNA can cause embryo-fetal harm when administered to a pregnant woman. There are no available data on TALZENNA use in pregnant women to inform a drug-associated risk. In an animal reproduction study, the administration of talazoparib to pregnant rats during the period of organogenesis caused fetal malformations and structural skeletal variations and embryo-fetal death at maternal exposures that were 0.24 times the AUC in patients receiving the recommended dose of 1 mg daily (see Data). Apprise pregnant women and females of reproductive potential of the potential risk to a fetus.

The background risk of major birth defects and miscarriage for the indicated population is unknown. In the general U.S. population, the estimated background risks of major birth defects and miscarriage in clinically recognized pregnancies are 2% to 4% and 15% to 20%, respectively.

Data
Animal Data
In an embryo-fetal development toxicity study, pregnant rats received oral doses of 0.015, 0.05, and 0.15 mg/kg/day talazoparib during the period of organogenesis. Talazoparib caused embryo-fetal death at doses ≥0.015 mg/kg/day (approximately 0.24 times the AUC in patients at the recommended dose of 1 mg daily). A dose of 0.015 mg/kg/day caused decreased fetal body weights and an increased incidence of fetal malformations (depressed eye bulge, small eye, split sternebra, and fused cervical vertebral arch) and structural variations including misshapen or incomplete ossification of the sternebra, skull, rib, and vertebra.

8.2 Lactation

Risk Summary
There are no data on the presence of talazoparib in human milk, the effects of the drug on milk production, or the effects of the drug on the breastfed child. Because of the potential for serious adverse reactions in a breastfed child from talazoparib, advise lactating women not to breastfeed during treatment with TALZENNA and for 1 month after the last dose.

8.3 Females and Males of Reproductive Potential

TALZENNA can cause fetal harm when administered to pregnant women [see Use in Specific Populations (8.1)].

Pregnancy Testing
Verify pregnancy status in females of reproductive potential prior to initiating TALZENNA treatment.

Contraception
Females
Advise females of reproductive potential to use effective contraception during treatment and for 7 months following the last dose of TALZENNA.

Males
Based on genotoxicity and animal reproduction studies, advise male patients with female partners of reproductive potential and pregnant partners to use effective contraception during treatment with TALZENNA and for 4 months following the last dose [see Use in Specific Populations (8.1), Nonclinical Toxicology (13.1)].

Infertility
Males
Based on animal studies, TALZENNA may impair fertility in males of reproductive potential [see Nonclinical Toxicology (13.1)].

8.4 Pediatric Use

The safety and effectiveness of TALZENNA have not been established in pediatric patients.

8.5 Geriatric Use

In clinical trials of TALZENNA enrolling 494 patients with advanced solid tumors who received TALZENNA 1 mg daily as a single agent, 85 (17%) patients were ≥65 years of age, and this included 19 (4%) patients who were ≥75 years old. There were 5 patients ≥85 years old. In the TALAPRO-2 trial, of 197 patients who received TALZENNA, 77% were ≥65 years of age, while 30% were ≥75 years of age. No overall differences in safety or effectiveness of TALZENNA were observed between these patients and younger patients.

8.6 Hepatic Impairment

No dosage modification is recommended for patients with hepatic impairment [see Clinical Pharmacology (12.3)].

8.7 Renal Impairment

Reduce the recommended dosage of TALZENNA in patients with moderate (CLcr 30 – 59 mL/min) and severe (CLcr 15 – 29 mL/min) renal impairment [see Dosage and Administration (2.7)]. Monitor patients with severe renal impairment for increased adverse reactions and modify the dosage as recommended for adverse reactions [see Dosage and Administration (2.5)].

No dose adjustment is recommended for patients with mild renal impairment (CLcr 60 – 89 mL/min). TALZENNA has not been studied in patients requiring hemodialysis.

11 DESCRIPTION

Talazoparib is an inhibitor of mammalian polyadenosine 5'-diphosphoribose (ADP-ribose) polymerase (PARP) enzymes. The chemical name of talazoparib tosylate is (8S,9R)-5-Fluoro-8-(4-fluorophenyl)-9-(1-methyl-1H-1,2,4-triazol-5-yl)-2,7,8,9-tetrahydro-3H-pyrido[4,3,2-de]phthalazin-3-one 4-methylbenzenesulfonate (1:1). The chemical formula of talazoparib tosylate is C26H22F2N6O4S, and the relative molecular mass is 552.56 Daltons. The chemical structure of talazoparib tosylate is shown below:

Talazoparib tosylate is a white to yellow solid. TALZENNA capsules for oral use are available as:

- 0.1 mg hard hypromellose (HPMC) capsule that contains 0.145 mg talazoparib tosylate equivalent to 0.1 mg talazoparib free base, or
- 0.25 mg HPMC capsule that contains 0.363 mg talazoparib tosylate equivalent to 0.25 mg talazoparib free base, or
- 0.35 mg HPMC capsule that contains 0.509 mg talazoparib tosylate equivalent to 0.35 mg talazoparib free base, or
- 0.5 mg HPMC capsule that contains 0.727 mg talazoparib tosylate equivalent to 0.5 mg talazoparib free base, or
- 0.75 mg HPMC capsule that contains 1.09 mg talazoparib tosylate equivalent to 0.75 mg talazoparib free base, or
- 1 mg HPMC capsule that contains 1.453 mg talazoparib tosylate equivalent to 1 mg talazoparib free base.

Inactive ingredients: silicified microcrystalline cellulose (sMCC). The capsule shells contain hypromellose (HPMC), yellow iron oxide, red iron oxide and titanium dioxide; and the printing ink contains shellac, black iron oxide, potassium hydroxide, ammonium hydroxide, and propylene glycol.

12 CLINICAL PHARMACOLOGY

12.1 Mechanism of Action

Talazoparib is an inhibitor of PARP enzymes, including PARP1 and PARP2, which play a role in DNA repair. In vitro studies with cancer cell lines that harbored defects in DNA repair genes, including BRCA1 and BRCA2, have shown that talazoparib-induced cytotoxicity may involve inhibition of PARP enzymatic activity and increased formation of PARP-DNA complexes resulting in DNA damage, decreased cell proliferation, and apoptosis. Talazoparib anti-tumor activity was observed in patient-derived xenograft breast cancer models bearing mutated BRCA1 or mutated BRCA2 or wild type BRCA1 and BRCA2.

12.2 Pharmacodynamics

The exposure-response relationship and time course of pharmacodynamic response for the safety and effectiveness of TALZENNA have not been fully characterized.

Cardiac Electrophysiology
At a dose of 1 mg (the recommended dosage for treatment of breast cancer), TALZENNA had no large QTc prolongation (i.e., >20 ms).

12.3 Pharmacokinetics

After administration of TALZENNA 1 mg orally once daily as a single agent (the recommended dosage for breast cancer), the mean [% coefficient of variation (CV%)] AUC and maximum observed plasma concentration (Cmax) of talazoparib at steady-state was 208 (37%) ng.hr/mL and 16.4 (32%) ng/mL, respectively. The mean (CV%) steady-state Ctrough was 3.53 (61%) ng/mL.

After administration of TALZENNA 0.5 mg orally once daily (the recommended dosage for prostate cancer) with enzalutamide, the mean (CV%) steady-state Ctrough ranged from 3.29 to 3.68 ng/mL (45% to 48%).

The pharmacokinetics (PK) of talazoparib is linear from 0.025 mg to 2 mg (2 times the recommended dose for breast cancer). The median accumulation ratio of talazoparib following 1 mg orally once daily is 2.3 to 5.2. Talazoparib plasma concentrations reached steady-state within 2 to 3 weeks when administered as a single agent and within 9 weeks when coadministered with enzalutamide.

Absorption
The median time to Cmax (Tmax) was generally between 1 to 2 hours after dosing.

Food Effect
Following a single TALZENNA 0.5 mg dose with high-fat, high-calorie food (approximately 800 to 1000 calories with 150, 250, and 500 to 600 calories from protein, carbohydrate, and fat, respectively), the mean Cmax was decreased by 46%, the median Tmax was delayed from 1 to 4 hours, and AUC was not affected.

Distribution
The mean apparent volume of distribution of talazoparib is 420 L. In vitro, protein binding of talazoparib is 74% and is independent of talazoparib concentration.

Elimination
The mean terminal plasma half-life (±standard deviation) is 90 (±58) hours and the mean apparent oral clearance (inter-subject variability) is 6.45 L/h (31%).

Metabolism
Talazoparib undergoes minimal hepatic metabolism. The identified metabolic pathways include mono-oxidation, dehydrogenation, cysteine conjugation of mono-desfluoro-talazoparib, and glucuronide conjugation.

Excretion
Excretion of talazoparib in urine was the major route of elimination. Approximately 68.7% (54.6% unchanged) of the total administered radiolabeled dose of talazoparib was recovered in urine, and 19.7% (13.6% unchanged) was recovered in feces.

Specific Populations
Age (18 to 88 years), sex, race (361 White, 41 Asian, 16 Black, 9 Others, and 63 Not Reported), body weight (36 to 162 kg), and mild to severe hepatic impairment had no clinically significant effect on the PK of talazoparib.

Patients with Renal Impairment
Mild (eGFR 60 – 89 mL/min/1.73 m^2) renal impairment had no clinically significant effect on talazoparib pharmacokinetics. Talazoparib steady-state total exposure (AUC) increased by 43% in subjects with moderate (eGFR 30 – 59 mL/min/1.73 m^2) renal impairment and 163% in patients with severe (eGFR 15 – 29 mL/min/1.73 m^2) renal impairment relative to subjects with normal renal function (eGFR ≥ 90 mL/min/1.73 m^2). Talazoparib steady-state peak concentration (Cmax) increased by 32% in subjects with moderate renal impairment and 89% in subjects with severe renal impairment, relative to subjects with normal renal function. Similar increases in AUC were observed with talazoparib when given with enzalutamide for patients with moderate and severe renal impairment. The PK of talazoparib has not been studied in patients requiring hemodialysis. There was no evidence of a relationship between the protein binding of talazoparib and renal function.

Drug Interaction Studies
Clinical Studies
Effect of P-gp Inhibitors: Coadministration of a P-gp inhibitor (itraconazole) with a single 0.5 mg dose of TALZENNA increased talazoparib AUC and Cmax by approximately 56% and 40%, respectively. Coadministration with the following other P-gp inhibitors: amiodarone, carvedilol, clarithromycin, itraconazole, and verapamil increased talazoparib exposure by 45%.

Coadministration with other P-gp inhibitors (including azithromycin, atorvastatin, diltiazem, felodipine, fluvoxamine, and quercetin) had no clinically significant effect on talazoparib pharmacokinetics.

Effect of P-gp Inducers: Coadministration of a P-gp inducer (rifampin) with a single 1 mg dose of TALZENNA increased talazoparib Cmax by 37% with no effect on talazoparib AUC.

Effect of Acid-Reducing Agents: Coadministration of acid-reducing agents including proton pump inhibitors (PPI), histamine receptor 2 antagonists (H2RA), or other acid-reducing agents has no effect on the absorption of talazoparib.

Enzalutamide: Coadministration of enzalutamide with TALZENNA increased talazoparib exposure approximately 2-fold.

In Vitro Studies
Transporters: Talazoparib is a substrate of P-gp and BCRP transporters, but not a substrate of OATP1B1, OATP1B3, OCT1, OCT2, OAT1, OAT3, BSEP, MATE1, or MATE2-K.

Talazoparib is not an inhibitor of P-gp, BCRP, OATP1B1, OATP1B3, OCT1, OCT2, OAT1, OAT3, BSEP, MATE1, or MATE2-K.

CYP Enzymes: Talazoparib is not an inhibitor of CYP1A2, CYP2B6, CYP2C8, CYP2C9, CYP2C19, CYP2D6, or CYP3A4/5.

Talazoparib is not an inducer of CYP1A2, CYP2B6, or CYP3A4.

UGT: Talazoparib is not an inhibitor of UGT isoforms (1A1, 1A4, 1A6, 1A9, 2B7, and 2B15).

13 NONCLINICAL TOXICOLOGY

13.1 Carcinogenesis, Mutagenesis, Impairment of Fertility

Carcinogenicity studies have not been conducted with talazoparib.

Talazoparib was clastogenic in an in vitro chromosomal aberration assay in human peripheral blood lymphocytes and in an in vivo bone marrow micronucleus assay in rats. This clastogenicity is consistent with genomic instability resulting from the primary pharmacology of talazoparib, indicating the potential for genotoxicity in humans. Talazoparib was not mutagenic in a bacterial reverse mutation (Ames) test.

Fertility studies in animals have not been conducted with talazoparib. In repeat-dose toxicity studies up to 3-months duration, talazoparib-related findings in the testis and epididymis at doses ≥0.04 mg/kg/day in rats and ≥0.01 mg/kg/day in dogs included decreased organ weights, luminal cellular debris, reduced sperm, and degeneration/atrophy. These doses in rats and dogs resulted in approximately 1.0 times and 0.2 times, respectively, the exposure (AUC) in humans at the recommended dose of 1 mg daily. Follicular atresia of the ovary was observed in rats at doses ≥1 mg/kg/day talazoparib, approximately 9.5 times the AUC in patients at the recommended dose of 1 mg daily.

14 CLINICAL STUDIES

14.1 Deleterious or Suspected Deleterious Germline BRCA-mutated HER2-negative Locally Advanced or Metastatic Breast Cancer

EMBRACA (NCT01945775) was an open-label study in which patients (N=431) with gBRCAm HER2-negative locally advanced or metastatic breast cancer were randomized 2:1 to receive TALZENNA 1 mg or healthcare provider's choice of chemotherapy (capecitabine, eribulin, gemcitabine, or vinorelbine) until disease progression or unacceptable toxicity. Randomization was stratified by prior lines of chemotherapy for metastatic disease (0 versus 1, 2, or 3), by triple-negative disease status [triple-negative breast cancer (TNBC) versus non-TNBC], and history of central nervous system (CNS) metastasis (yes versus no).

Patients received no more than 3 prior cytotoxic chemotherapy regimens for their metastatic or locally advanced disease. Patients were required to have received treatment with an anthracycline and/or a taxane (unless contraindicated) in the neoadjuvant, adjuvant, and/or metastatic treatment setting. First-line treatment for advanced or metastatic disease with no prior adjuvant chemotherapy was allowed if the investigator determined that 1 of the 4 chemotherapy choices in the control arm would be an appropriate treatment option for the patient. Patients with prior platinum therapy for advanced disease were required to have no evidence of disease progression during platinum therapy. No prior treatment with a PARP inhibitor was permitted. Of the 431 patients randomized in the EMBRACA study, 408 (95%) were centrally confirmed to have a deleterious or suspected deleterious gBRCAm using a clinical trial assay; out of which 354 (82%) were confirmed using the BRACAnalysis CDx®. BRCA mutation status [breast cancer susceptibility gene 1 (BRCA1)-positive or breast cancer susceptibility gene 2 (BRCA2)-positive] was similar across both treatment arms.

The median age of patients treated with TALZENNA was 46 years (range 28 to 84) and 51 years (range 24 to 89) among patients treated with chemotherapy. Among all randomized patients, 1% versus 2% were males, 67% versus 75% were White; 11% versus 11% were Asian, and 4% versus 1% were Black or African American in the TALZENNA and chemotherapy arms, respectively. Almost all patients (98%) in both arms had an Eastern Cooperative Oncology Group (ECOG) performance status of 0 or 1. Approximately 56% of patients had estrogen receptor-positive and/or progesterone receptor-positive disease; 44% of patients had triple-negative disease, and the proportions were balanced across both treatment arms. Fifteen percent (15%) of patients in the TALZENNA arm and 14% of patients in the chemotherapy arm had a history of CNS metastases. Ninety-one percent (91%) of patients in the TALZENNA arm had received prior taxane therapy, and 85% had received prior anthracycline therapy in any setting. Sixteen percent (16%) of patients in the TALZENNA arm and 21% of patients in the chemotherapy arm had received prior platinum treatment in any setting. The median number of prior cytotoxic regimens for patients with advanced breast cancer was one; 38% received no prior cytotoxic regimens for advanced or metastatic disease, 37% received one, 20% received two, and 5% received three or more prior cytotoxic regimens.

The major efficacy outcome measure was progression-free survival (PFS) evaluated according to Response Evaluation Criteria in Solid Tumors (RECIST) version 1.1, as assessed by blinded independent central review (BICR). A statistically significant improvement in PFS was demonstrated for TALZENNA compared to chemotherapy. A sensitivity analysis of investigator-assessed PFS was consistent with the BICR-assessed PFS results. Consistent PFS results were observed across patient subgroups defined by study stratification factors (prior lines of chemotherapy, TNBC status, and history of CNS metastases). Efficacy data from the EMBRACA study are summarized in Table 9, and the Kaplan-Meier curves for PFS are shown in Figure 1 and final overall survival (OS) in Figure 2.

Table 9. Efficacy Results – EMBRACA Study
 | TALZENNA | Chemotherapy
PFS by BICR | N=287 | N=144
Disease progression or deaths, n (%) | 186 (65) | 83 (58)
Median months (95% CI) | 8.6 (7.2, 9.3) | 5.6 (4.2, 6.7)
Hazard ratio (95% CI) [Hazard ratio is estimated from a Cox proportional hazards model stratified by prior use of chemotherapy for metastatic disease (0 versus 1, 2, or 3), by triple-negative disease status [triple-negative breast cancer (TNBC) versus non-TNBC], and by history of central nervous system metastasis (yes versus no) and is relative to overall chemotherapy with <1 favoring talazoparib.] | 0.54 (0.41, 0.71)
p-value [p-values (2-sided) from the log-rank test stratified by number of prior cytotoxic chemotherapy regimens, triple-negative status and history of central nervous system metastasis.] | p<0.0001
Patients with Measurable Disease by Investigator [Conducted in ITT population with measurable disease at baseline.] | N=219 | N=114
ORR, % (95% CI) [Response rate based on confirmed responses.] | 50.2 (43.4, 57.0) | 18.4 (11.8, 26.8)
Median [Median estimated from Kaplan-Meier probabilities.] DOR months (95% CI) | 6.4 (5.4, 9.5) | 3.9 (3.0, 7.6)
OS | N=287 | N=144
Deaths, n (%) | 216 (75) | 108 (75)
Median months (95% CI) | 19.3 (16.6, 22.5) | 19.5 (17.4, 22.4)
Hazard ratio (95% CI) | 0.85 (0.67, 1.07)
p-value | p=0.1693
Abbreviations: BICR=blinded independent central review; CI=confidence interval; DOR=duration of response; ITT=intent-to-treat; N=number of patients; ORR=objective response rate; OS=overall survival; PFS=progression-free survival.

Figure 1. Kaplan-Meier Curves of PFS – EMBRACA Study

Abbreviation: PFS=progression-free survival.

Figure 2. Kaplan-Meier Curves of OS – EMBRACA Study (ITT Population)

Abbreviations: ITT=intent-to-treat; OS=overall survival.

14.2 HRR Gene-mutated mCRPC

The efficacy of TALZENNA with enzalutamide was evaluated in TALAPRO-2 (NCT03395197), a randomized, double-blind, placebo-controlled, multi-cohort trial in which 399 patients with HRR gene-mutated (HRRm) mCRPC were randomized 1:1 to receive enzalutamide 160 mg daily plus either TALZENNA 0.5 mg or placebo daily until unacceptable toxicity or disease progression. Mutation status of HRR genes was determined prospectively using solid tumor tissue or circulating tumor DNA (ctDNA)-based next generation sequencing assays. Patients were required to have a mutation in at least one of 12 genes involved directly or indirectly in the HRR pathway (ATM, ATR, BRCA1, BRCA2, CDK12, CHEK2, FANCA, MLH1, MRE11A, NBN, PALB2, or RAD51C). All patients received a GnRH analog or had prior bilateral orchiectomy and needed to have progressed on prior androgen deprivation therapy. Prior treatment with a CYP17 inhibitor or docetaxel for metastatic castration-sensitive prostate cancer (mCSPC) was permitted. Randomization was stratified by previous treatment with a CYP17 inhibitor or docetaxel (yes/no).

The median age was 70 years (range: 41 to 90); 100% were male; 68% were White, 21% Asian, 2.8% Black, 0.8% Other, 7% unknown/not reported; 12% were Hispanic/Latino; and baseline ECOG performance status was 0 (62%) or 1 (38%). Thirty-nine percent of patients had bone-only disease; 15% had visceral disease. In the mCSPC setting, 29% percent of patients had received docetaxel and 9% had received a prior CYP17 inhibitor. The most commonly mutated HRR genes (>5%), including co-occurring mutations, were: BRCA2 (34%), ATM (22%), CDK12 (19%), CHEK2 (18%), and BRCA1 (6%).

The major efficacy outcome measure was radiographic progression-free survival (rPFS) evaluated according to RECIST, version 1.1 and Prostate Cancer Working Group (PCWG3) (bone) criteria, assessed by BICR. An additional efficacy outcome measure was OS.

A statistically significant improvement in rPFS and OS were demonstrated in patients randomized to TALZENNA with enzalutamide compared with placebo with enzalutamide. Efficacy results are presented in Table 10, and Figures 3 and 4.

Table 10. Efficacy Results – TALAPRO-2 (HRR Gene-mutated mCRPC)
 | TALZENNA with Enzalutamide; N=200 |  | Placebo with Enzalutamide; N=199
Radiographic Progression-free Survival (rPFS) by BICR
Number of events, n (%) | 66 (33) |  | 104 (52)
Median months (95% CI) | NR (21.9, NR) |  | 13.8 (11.0, 16.7)
Hazard ratio (95% CI) [Hazard ratio and CI are based on Cox PH model stratified by previous treatment for CSPC.] | 0.45 (0.33, 0.61)
p-value [p-value (2-sided) is based on log-rank test stratified by previous treatment for CSPC.] | p<0.0001
Overall Survival (OS)
Deaths, n (%) | 93 (47) | 126 (63)
Median months (95% CI) | 45.1 (35.4, NR) | 31.1 (27.3, 35.4)
Hazard ratio (95% CI) | 0.62 (0.48, 0.81)
p-value | p=0.0005
Abbreviations: BICR=blinded independent central review; CI=confidence interval; CSPC=castration-sensitive prostate cancer; HRR=homologous recombination repair; mCRPC=metastatic castration-resistant prostate cancer; N=number of patients; NR=not reached.

Figure 3. Kaplan-Meier Curves of rPFS - TALAPRO-2 (HRR Gene-mutated mCRPC)

Abbreviations: HRR=homologous recombination repair; mCRPC=metastatic castration-resistant prostate cancer; rPFS=radiographic progression-free survival.

Figure 4. Kaplan-Meier Curves of OS – TALAPRO-2 (HRR Gene-mutated mCRPC)

Abbreviations: HRR=homologous recombination repair; mCRPC=metastatic castration-resistant prostate cancer; OS=overall survival.

Exploratory subgroup analyses of rPFS and OS for patients with BRCA-mutated (BRCAm) and non-BRCAm HRRm are presented in Table 11.

Table 11. Exploratory rPFS and OS Subgroup Analyses by BRCAm Status for TALAPRO-2 (HRR Gene-mutated mCRPC)
 | BRCAm |  | Non-BRCAm HRRm [Includes 4 patients who were incorrectly randomized in the HRRm stratum who did not have HRR gene mutations.]
 | TALZENNA with Enzalutamide; N=71 | Placebo with Enzalutamide; N=84 | TALZENNA with Enzalutamide; N=129 | Placebo with Enzalutamide; N=115
rPFS
Number of events, n (%) | 15 (21) | 54 (64) | 51 (40) | 50 (43)
Median months (95% CI) | NR (NR, NR) | 11.0 (8.3, 11.1) | 24.7 (16.4, NR) | 16.7 (13.8, 27.7)
Hazard ratio (95% CI) | 0.20 (0.11, 0.36) |  | 0.74 (0.50, 1.09)
Overall Survival (OS)
Deaths, n (%) | 30 (42) | 56 (67) | 63 (49) | 70 (61)
Median months (95% CI) | NR; (35.4, NR) | 28.5; (24.5, 34.4) | 42.4; (34.2, NR) | 32.6; (28.0, 42.2)
Hazard ratio (95% CI) [Hazard ratio and CI are based on Cox PH model unstratified by previous treatment for CSPC.] | 0.48 (0.31, 0.75) |  | 0.71 (0.51, 1.00)
Abbreviations: BRCAm=breast cancer susceptibility gene-mutated; CI=confidence interval; CSPC=castration-sensitive prostate cancer; HRRm=homologous recombination repair gene-mutated; NR=not reached; rPFS=radiographic progression-free survival.

16 HOW SUPPLIED/STORAGE AND HANDLING

TALZENNA is supplied in strengths and package configurations as described in Table 12:

Table 12. TALZENNA Capsules
Package Configuration | Capsule Strength (mg) | NDC | Print
Bottles of 30 capsules | 0.1 | NDC 0069-1031-30 | White cap (printed with “Pfizer” in black) and a white body (printed with “TLZ 0.1” in black).
Bottles of 30 capsules | 0.25 | NDC 0069-0296-30 | Ivory cap (printed with “Pfizer” in black) and a white body (printed with “TLZ 0.25” in black).
Bottles of 30 capsules | 0.35 | NDC 0069-1235-30 | Ivory cap (printed with “Pfizer” in black) and an ivory body (printed with “TLZ 0.35” in black).
Bottles of 30 capsules | 0.5 | NDC 0069-1501-30 | Light pink cap (printed with “Pfizer” in black) and a white body (printed with “TLZ 0.5” in black).
Bottles of 30 capsules | 0.75 | NDC 0069-1751-30 | Light orange cap (printed with “Pfizer” in black) and a white body (printed with “TLZ 0.75” in black).
Bottles of 30 capsules | 1 | NDC 0069-1195-30 | Light red cap (printed with “Pfizer” in black) and a white body (printed with “TLZ 1” in black).

Storage

Store at 20°C to 25°C (68°F to 77°F); excursions permitted between 15°C to 30°C (59°F to 86°F). [See USP Controlled Room Temperature].

17 PATIENT COUNSELING INFORMATION

Advise the patient to read the FDA-approved patient labeling (Patient Information).

- MDS/AML: Advise patients to contact their healthcare provider if they experience weakness, feeling tired, fever, weight loss, frequent infections, bruising, bleeding easily, breathlessness, blood in urine or stool, and/or laboratory findings of low blood cell counts, or a need for blood transfusions. This may be a sign of hematological toxicity or a more serious uncommon bone marrow problem called MDS or AML, which have been reported in patients who received PARP inhibitors [see Warnings and Precautions (5.1)].
- Myelosuppression: Advise patients that TALZENNA may affect hematopoiesis and can cause anemia, leukopenia/neutropenia, and/or thrombocytopenia [see Warnings and Precautions (5.2)].
- Administration Instructions: Advise patients that TALZENNA can be taken once daily with or without food. Instruct patients that if they miss a dose of TALZENNA, they should take their next normal dose at the usual time. Also advise patients to swallow each capsule whole, and that capsules must not be opened or dissolved [see Dosage and Administration (2.4)].
- Embryo-Fetal Toxicity: Advise females to inform their healthcare provider if they are pregnant or become pregnant. Inform female patients of the risk to a fetus and potential loss of the pregnancy [see Use in Specific Populations (8.1)]. Advise females of reproductive potential to use effective contraception during treatment with TALZENNA and for 7 months after the last dose. Advise male patients with female partners of reproductive potential or who are pregnant to use effective contraception during treatment and for 4 months after receiving the last dose of TALZENNA [see Warnings and Precautions (5.3), Use in Specific Populations (8.1, 8.3)].
- Lactation: Advise patients not to breastfeed while taking TALZENNA and for 1 month after receiving the last dose [see Use in Specific Populations (8.2)].

This product's labeling may have been updated. For the most recent prescribing information, please visit http://www.pfizer.com.

LAB-1271-9.0

PATIENT INFORMATION
TALZENNA® (Tal-ZEN-ah)
(talazoparib)
capsules

What is the most important information I should know about TALZENNA?
TALZENNA may cause serious side effects, including:

- Bone marrow problems called Myelodysplastic Syndrome (MDS) or Acute Myeloid Leukemia (AML). Some people who have cancer and who have received previous treatment with chemotherapy or certain other medicines for their cancer have developed MDS or AML during or after treatment with TALZENNA. MDS or AML may lead to death. If you develop MDS or AML, your healthcare provider will stop treatment with TALZENNA.
  Symptoms of low blood cell counts are common during treatment with TALZENNA, but can be a sign of serious problems, including MDS or AML. Tell your healthcare provider if you have any of the following symptoms during treatment with TALZENNA:

○ weakness

○ weight loss

○ fever

○ frequent infections

○ blood in urine or stool

○ shortness of breath

○ feeling very tired

○ bruising or bleeding more easily

Your healthcare provider will do blood tests to check your blood cell counts:

○ every month during treatment with TALZENNA.

○ weekly if you have low blood cell counts that last a long time.

Your healthcare provider may change your dose, temporarily stop, or permanently stop treatment with TALZENNA if you get certain side effects.

See “What are the possible side effects of TALZENNA?” below for other side effects of TALZENNA.

What is TALZENNA?
TALZENNA is a prescription medicine used:

- alone to treat adults with human epidermal growth factor receptor 2 (HER2)-negative breast cancer:
  - who have a certain type of an abnormal inherited BRCA gene, and
  - whose cancer has spread to other parts of the body (locally advanced or metastatic).
Your healthcare provider will perform a test to make sure that TALZENNA is right for you.
- in combination with a medicine called enzalutamide, to treat adults with prostate cancer
  - with certain abnormal inherited or acquired genes called homologous recombination repair (HRR genes) and
  - which no longer responds to hormone therapy or surgical treatment to lower testosterone and has spread to other parts of the body (metastatic).
Your healthcare provider will perform a test to make sure that TALZENNA is right for you.

It is not known if TALZENNA is safe and effective in children.

Before taking TALZENNA, tell your healthcare provider about all of your medical conditions, including if you:

- have kidney problems.
- are pregnant or plan to become pregnant. TALZENNA can harm your unborn baby and may cause loss of pregnancy (miscarriage). You should not become pregnant during treatment with TALZENNA.
  Females who are able to become pregnant:
  - Your healthcare provider may do a pregnancy test before you start treatment with TALZENNA.
  - You should use effective birth control (contraception) during treatment with TALZENNA and for 7 months after the last dose of TALZENNA. Talk to your healthcare provider about forms of birth control that may be right for you.
  - Tell your healthcare provider right away if you are pregnant or think you are pregnant during treatment with TALZENNA.
Males with female partners who are pregnant or are able to become pregnant:
  1. You should use effective birth control during treatment with TALZENNA and for 4 months after the last dose of TALZENNA.
- are breastfeeding or plan to breastfeed. It is not known if TALZENNA passes into your breast milk. Do not breastfeed during treatment with TALZENNA and for 1 month after the last dose of TALZENNA. Talk to your healthcare provider about the best way to feed your baby during this time.

Tell your healthcare provider about all the medicines you take, including prescription and over-the-counter medicines, vitamins, and herbal supplements. Taking TALZENNA with certain other medicines can affect how TALZENNA works and may cause side effects.
Know the medicines you take. Keep a list of your medicines and show it to your healthcare provider and pharmacist when you get a new medicine.

How should I take TALZENNA?

- Take TALZENNA exactly as your healthcare provider tells you.
- Do not change your dose or stop taking TALZENNA without first talking with your healthcare provider.
- If you are prescribed TALZENNA for breast cancer, take TALZENNA 1 time a day.
- If you are prescribed TALZENNA for prostate cancer:
  - Take TALZENNA with enzalutamide 1 time a day.
  - You should start or continue a gonadotropin-releasing hormone (GnRH) analog therapy during your treatment with TALZENNA and enzalutamide unless you have had a surgery to lower the amount of testosterone in your body (surgical castration).
- Take TALZENNA with or without food.
- Swallow TALZENNA capsules whole. Do not dissolve or open TALZENNA capsules.
- If you vomit or miss a dose of TALZENNA, take your next dose at your regular time. Do not take an extra dose to make up for a missed dose.

What are the possible side effects of TALZENNA?

TALZENNA may cause serious side effects, including:

- See “What is the most important information I should know about TALZENNA?”

The most common side effects of TALZENNA when taken alone include:

- decreased red blood cell counts
- decreased white blood cell counts
- tiredness or weakness
- decreased platelet counts
- increased blood sugar levels
- increased liver function tests
- nausea

- headache
- decreased blood calcium levels
- vomiting
- hair loss
- diarrhea
- decreased appetite

The most common side effects of TALZENNA when taken in combination with enzalutamide include:

- decreased red blood cell counts
- decreased white blood cell counts
- tiredness or weakness
- decreased platelet counts
- decreased calcium in the blood
- nausea
- decreased appetite
- decreased sodium in the blood

- decreased phosphate in the blood
- bone injuries
- decreased magnesium in the blood
- dizziness
- increased bilirubin in the blood
- decreased potassium in the blood
- changes in your sense of taste

TALZENNA may cause fertility problems in males. This may affect your ability to father a child. Talk to your healthcare provider if this is a concern for you.

These are not all of the possible side effects of TALZENNA.

Call your doctor for medical advice about side effects. You may report side effects to FDA at 1-800-FDA-1088.

How should I store TALZENNA?

- Store TALZENNA at 68°F to 77°F (20°C to 25°C).

Keep TALZENNA and all medicines out of the reach of children.

General information about the safe and effective use of TALZENNA.
Medicines are sometimes prescribed for purposes other than those listed in a Patient Information leaflet. Do not use TALZENNA for a condition for which it is not prescribed. Do not give TALZENNA to other people, even if they have the same symptoms that you have. It may harm them. You can ask your healthcare provider or pharmacist for information about TALZENNA that is written for health professionals.

What are the ingredients in TALZENNA?
Active ingredient: talazoparib tosylate
Inactive ingredients: silicified microcrystalline cellulose (sMCC). The capsule shells contain hypromellose (HPMC), yellow iron oxide, red iron oxide and titanium dioxide. The printing ink contains shellac, black iron oxide, potassium hydroxide, ammonium hydroxide, and propylene glycol.

For more information, go to www.pfizer.com or call 1-800-438-1985.
LAB-1272-6.0

This Patient Information has been approved by the U.S. Food and Drug Administration. Revised: 6/2025

PRINCIPAL DISPLAY PANEL - 0.25 mg Capsule Bottle Label

Pfizer
NDC 0069-0296-30

Talzenna®
(talazoparib) capsules

0.25 mg

30 Capsules
Rx only

PRINCIPAL DISPLAY PANEL - 0.25 mg Capsule Bottle Carton

Pfizer
NDC 0069-0296-30

Talzenna®
(talazoparib)
capsules

0.25 mg

30 Capsules
Rx only

PRINCIPAL DISPLAY PANEL - 1 mg Capsule Bottle Label

Pfizer
NDC 0069-1195-30

Talzenna®
(talazoparib) capsules

1 mg

30 Capsules
Rx only

PRINCIPAL DISPLAY PANEL - 1 mg Capsule Bottle Carton

Pfizer
NDC 0069-1195-30

Talzenna®
(talazoparib)
capsules

1 mg

30 Capsules
Rx only

PRINCIPAL DISPLAY PANEL - 0.5 mg Capsule Bottle Label

Pfizer
NDC 0069-1501-30

Talzenna®
(talazoparib) capsules

0.5 mg

30 Capsules
Rx only

PRINCIPAL DISPLAY PANEL - 0.5 mg Capsule Bottle Carton

Pfizer
NDC 0069-1501-30

Talzenna®
(talazoparib)
capsules

0.5 mg

30 Capsules
Rx only

PRINCIPAL DISPLAY PANEL - 0.75 mg Capsule Bottle Label

Pfizer
NDC 0069-1751-30

Talzenna®
(talazoparib) capsules

0.75 mg

30 Capsules
Rx only

PRINCIPAL DISPLAY PANEL - 0.75 mg Capsule Bottle Carton

Pfizer
NDC 0069-1751-30

Talzenna®
(talazoparib)
capsules

0.75 mg

30 Capsules
Rx only

PRINCIPAL DISPLAY PANEL - 0.1 mg Capsule Bottle Label

Pfizer
NDC 0069-1031-30

Talzenna®
(talazoparib) capsules

0.1 mg

30 Capsules
Rx only

PRINCIPAL DISPLAY PANEL - 0.1 mg Capsule Bottle Carton

Pfizer
NDC 0069-1031-30

Talzenna®
(talazoparib)
capsules

0.1 mg

30 Capsules
Rx only

PRINCIPAL DISPLAY PANEL - 0.35 mg Capsule Bottle Label

Pfizer
NDC 0069-1235-30

Talzenna®
(talazoparib) capsules

0.35 mg

30 Capsules
Rx only

PRINCIPAL DISPLAY PANEL - 0.35 mg Capsule Bottle Carton

Pfizer
NDC 0069-1235-30

Talzenna®
(talazoparib)
capsules

0.35 mg

30 Capsules
Rx only